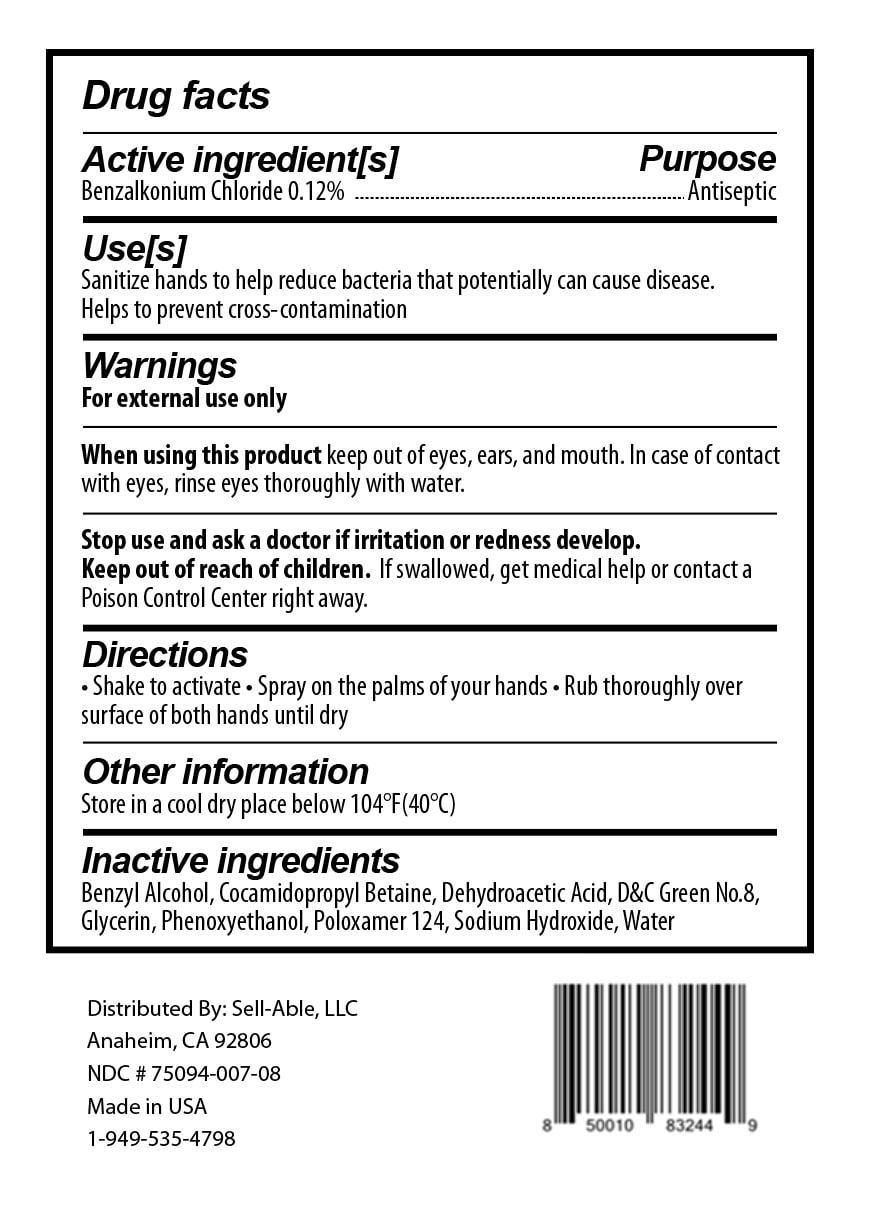 DRUG LABEL: Hand Sanitizer
NDC: 75094-007 | Form: SPRAY
Manufacturer: Sell-Able LLC
Category: otc | Type: HUMAN OTC DRUG LABEL
Date: 20200531

ACTIVE INGREDIENTS: BENZALKONIUM CHLORIDE 12 g/100 mL
INACTIVE INGREDIENTS: DEHYDROACETIC ACID; GLYCERIN; PHENOXYETHANOL; WATER; BENZYL ALCOHOL; COCAMIDOPROPYL BETAINE; D&C GREEN NO. 8; CITRIC ACID MONOHYDRATE; SODIUM HYDROXIDE; POLOXAMER 124

This is a hand sanitizer manufactured according to the Temporary Policy for Preparation of Certain Alcohol-Based Hand Sanitizer Products During the Public Health Emergency (CoViD-19); Guidance for Industry.

The hand sanitizer is manufactured using only the following United States Pharmacopoeia (USP) grade ingredients in the preparation of the product (percentage in final product formulation) consistent with World Health Organization (WHO) recommendations:

1. Isopropyl Alcohol (75%, v/v) in an aqueous solution denatured according to Alcohol and Tobacco Tax and Trade Bureau regulations in 27 CFR part 20.
2. Glycerol (1.45% v/v).
3. Hydrogen peroxide (0.125% v/v).
4. Sterile distilled water or boiled cold water.

The firm does not add other active or inactive ingredients. Different or additional ingredients may impact the quality and potency of the product.

Active Ingredient(s)

BENZALKONIUM CHLORIDE .12 g/100mL

Purpose

Antiseptic, Hand Sanitizer

Use

Hand Sanitizer to help reduce bacteria that potentially can cause disease. Helps to prevent cross-contamination

Warnings

For external use only.

When using this product

- Do not use in or near eyes

Stop use and ask a doctor if irritation or redness develop.

Keep out of reach of children. If swallowed, get medical help or contact a Poison Control Center immediately.

Other information

- Store in a cool dry place below 104 degress F (40C)

Inactive ingredients

GLYCERIN (UNII: PDC6A3C0OX)
PHENOXYETHANOL (UNII: HIE492ZZ3T)
DEHYDROACETIC ACID (UNII: 2KAG279R6R)
CITRIC ACID MONOHYDRATE (UNII: 2968PHW8QP)
BENZYL ALCOHOL (UNII: LKG8494WBH)
SODIUM HYDROXIDE (UNII: 55X04QC32I)
WATER (UNII: 059QF0KO0R)
COCAMIDOPROPYL BETAINE (UNII: 5OCF3O11KX)
POLOXAMER 124 (UNII: 1S66E28KXA)
D&C GREEN NO. 8 (UNII: I2W85YOX9L)

Directions

- Receive a small amount of foam into palm of hand.
- Rub thoroughly over all surfaces of both hands
- Rub hands together until dry.